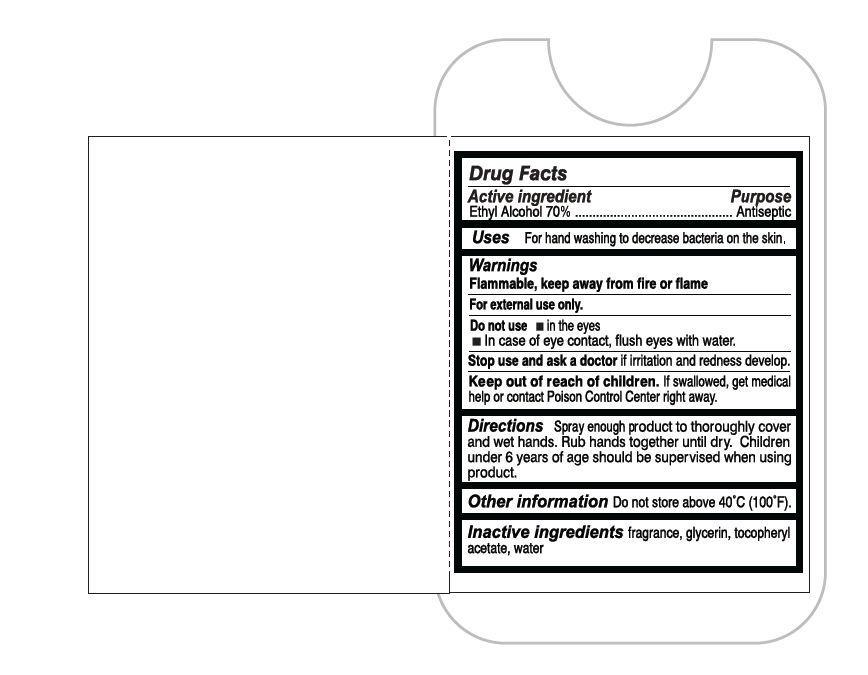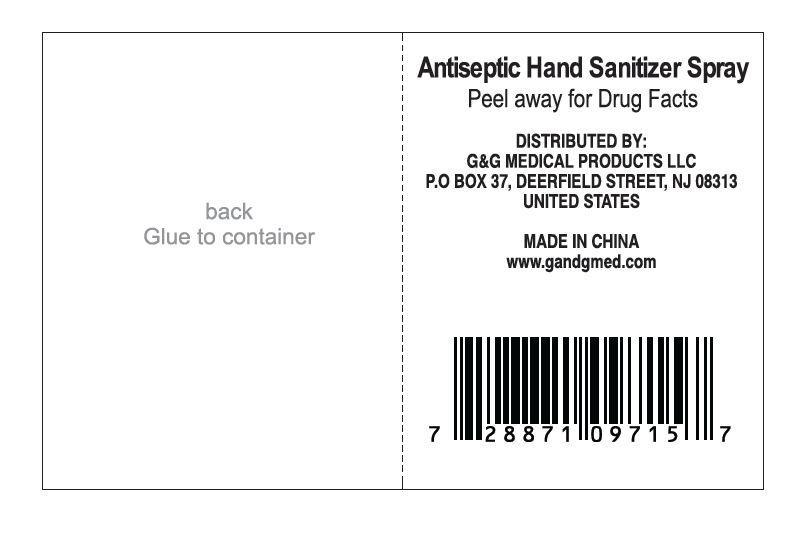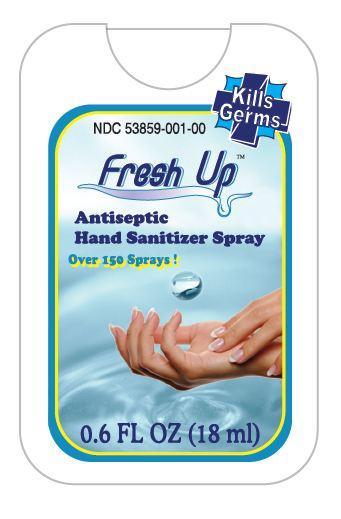 DRUG LABEL: Fresh Up Antiseptic Hand
NDC: 53859-001 | Form: SPRAY
Manufacturer: G&G Medical Products LLC
Category: otc | Type: HUMAN OTC DRUG LABEL
Date: 20121108

ACTIVE INGREDIENTS: ALCOHOL 70 mL/100 mL
INACTIVE INGREDIENTS: GLYCERIN; .ALPHA.-TOCOPHEROL ACETATE; WATER

Fresh Up Antiseptic Hand Spray

Active ingredient

Ethyl Alcohol 70 percent

Purpose

Antiseptic

Uses

For hand washing to decrease bacteria on the skin.

Warnings

Flammable, keep away from fire or flame

For external use only.

Do not use

- in the eyes
- In case of eye contact, flush eyes with water.

Stop use and ask a doctor if irritation and redness develop.

Keep out of reach of children.

If swallowed, get medical help or contact Poison Control Center right away.

Directions

Spray enough product to thoroughly cover and wet hands. Rub hands together until dry. Children under 6 years of age should be supervised when using product.

Other information

Do not store above 40 degree Celsius (100 degree Fahrenheit).

Inactive ingredients

fragrance, glycerin, tocopheryl acetate, water

Package labeling

Kills Germs

NDC 53859-001-00

Fresh Up TM

Antiseptic Hand Sanitizer Spray

Over 150 Sprays!

0.6 FL OZ (18 ml)

Antiseptic Hand Sanitizer Spray

Peel away for Drug Facts

DISTRIBUTED BY:
G AND G MEDICAL PRODUCTS, LLC
P.O BOX 37, DEERFIELD STREET, NJ 08313
UNITED STATES

MADE IN CHINA
www.gandgmed.com